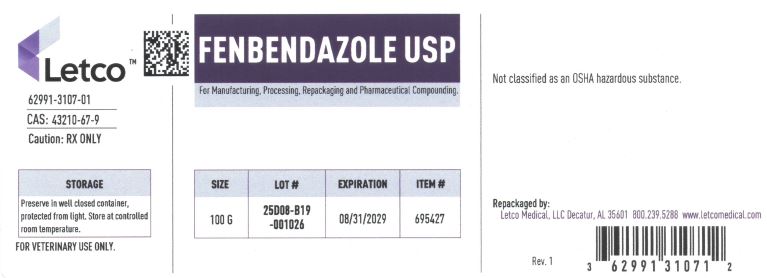 DRUG LABEL: Fenbendazole
NDC: 62991-3107 | Form: POWDER
Manufacturer: LETCO MEDICAL, LLC
Category: other | Type: BULK INGREDIENT - ANIMAL DRUG
Date: 20250627

ACTIVE INGREDIENTS: FENBENDAZOLE 1 g/1 g

Fenbendazole USP

PACKAGE LABEL

Fenbendazole USP 100g